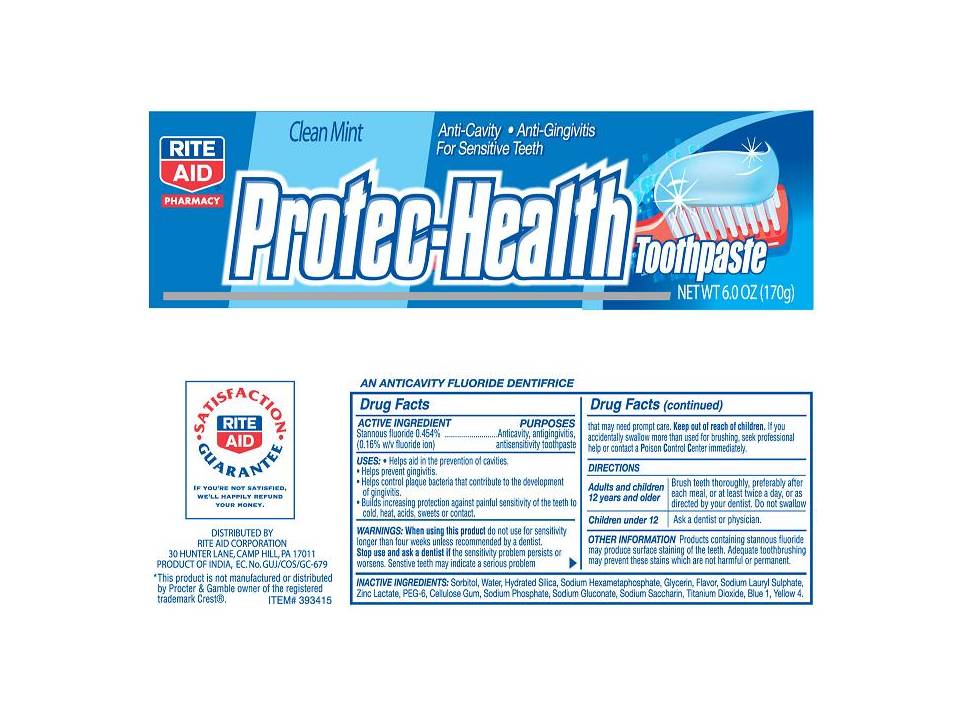 DRUG LABEL: Rite Aid Anti-Cavity, Anti-Gingivitis 
NDC: 11822-0001 | Form: PASTE
Manufacturer: Rite Aid
Category: otc | Type: HUMAN OTC DRUG LABEL
Date: 20101208

ACTIVE INGREDIENTS: Stannous Fluoride 4.54 mg/1 g
INACTIVE INGREDIENTS: SORBITOL; WATER; HYDRATED SILICA; SODIUM POLYMETAPHOSPHATE; GLYCERIN; SODIUM LAURYL SULFATE; ZINC LACTATE; POLYETHYLENE GLYCOL 300; CROSCARMELLOSE SODIUM; SODIUM PHOSPHATE; SODIUM GLUCONATE; SACCHARIN SODIUM ; TITANIUM DIOXIDE; FD&C BLUE NO. 1; FERRIC OXIDE YELLOW

Rite Aid Protec-Health Anti-Cavity, Anti-Gingivitis Toothpaste

Active Ingredient

STANNOUS FLUORIDE 0.454%................ANTICAVITY, ANTIGINGIVITIS
(.016% WITH FLUORIDE ION) antisensitivity toothpaste

USE

Helps aid in the prevention of cavities.

- Helps prevent gingivitis.
- Helps control plaque bacteria that contribute to the development of gingivitis.
- Builds increasing protection against painful sensitivity of the health to cold, heat, acids, sweets or contact.

When using this product do not use for sensitivity

longer than four weeks unless recommended by dentist.

Stop use and ask a dentist if the sensitivity problem persists or

worsens. Sensitive teeth may indicate a serious problem.

Directions

Adults and children Brush teeth thoroughly, preferably after

12 years and older each meal, or at least twice a day, or as

directed by your dentist. Do not swallow.

Children under 12 Ask a dentist or physician

OTHER INFORMATION Products containing stannous fluoride

may produce surface staining of the teeth. Adequate toothbrushing

may prevent these stains which are not harmful or perment.

Inactive ingredients:

Sorbitol, Water, Hydrated Silica, Sodium Hexametaphosphate, Glycerin, Sodium Lauryl Sulfate, Zinc Lactate, PEG-6, Cellulose Gum, Sodium Phosphate, Sodium Gluconate, Saccharin Sodium, Titanium Dioxide, Blue 1, Yellow 4